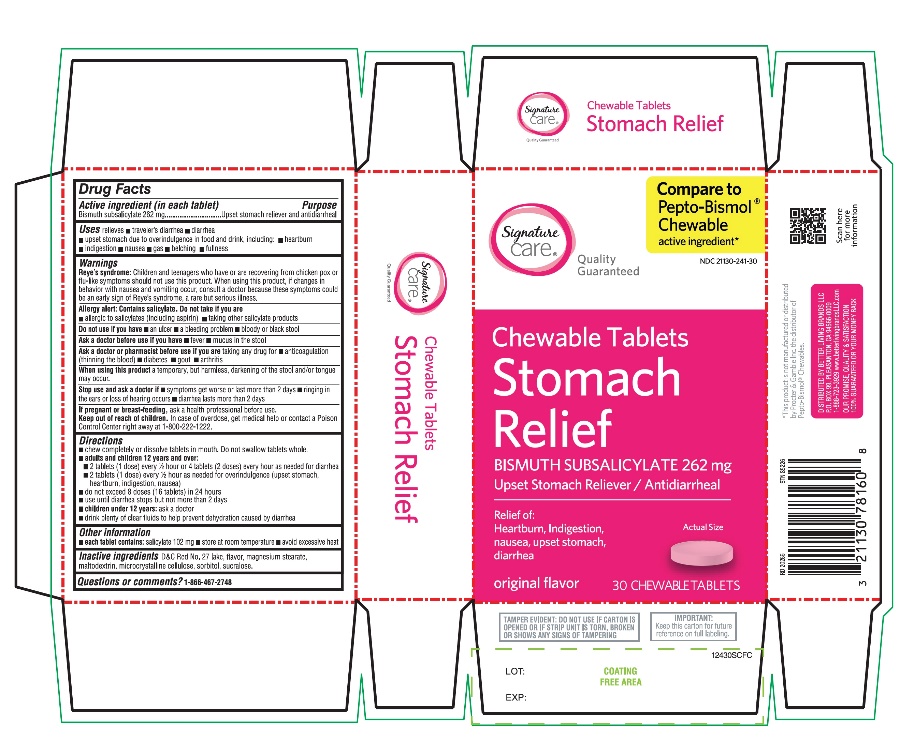 DRUG LABEL: Stomach Relief
NDC: 21130-241 | Form: TABLET, CHEWABLE
Manufacturer: SAFEWAY
Category: otc | Type: HUMAN OTC DRUG LABEL
Date: 20251029

ACTIVE INGREDIENTS: BISMUTH SUBSALICYLATE 262 mg/1 1
INACTIVE INGREDIENTS: D&C RED NO. 27; MAGNESIUM STEARATE; MALTODEXTRIN; MICROCRYSTALLINE CELLULOSE; SORBITOL; SUCRALOSE

Stomach Relief Bismuth Subsalicylate 262 mg Chewable Tablets 30 Counts

Drug Facts

Active ingredient (in each chewable tablet)

Bismuth subsalicylate 262 mg

Purpose

Antidiarrheal/ upset stomach reliever

Uses

relieves

- travelers' diarrhea
- diarrhea
- upset stomach due to overindulgence in food and drink, including
  - heartburn
  - indigestion
  - nausea
  - gas
  - belching
  - fullness

Warnings

Reye's syndrome

Children and teenagers who have or are recovering from chicken pox or flu-like symptoms should not use this product. When using this product, if changes in behavior with nausea or vomiting occur, consult a doctor because these symptoms could be an early sign of Reye's syndrome, a rare but serious illness.

Allergy alert

Do not use if you are

- allergic to salicylate (including aspirin)
- taking other salicylate products

Do not use ifyou have

- an ulcer
- a bleeding problem
- bloody or black stool

Ask a doctor before use if you have

- fever
- mucus in the stool

Ask a doctor or pharmacist before use if you aretaking any drug for

- anticoagulation (thinning of the blood)
- diabetes
- gout
- arthritis

WHEN USING

When using this producta temporary, but harmless, darkening of the stool and/or tongue may occur

Stop use and ask a doctor if

- symptoms get worse or last more than 2 days
- ringing in the ears or loss of hearing occurs
- diarrhea lasts more than 2 days

PREGNANCY OR BREAST FEEDING

If pregnant or breastfeeding,ask a health professional before use.

Keep out of reach of children.In case of overdose, get medical help or contact a Poison Control Center immediately at 1-800-222-1222

Directions

- chew completely or dissolve tablets in mouth. Do not swallow tablets whole.
- adults and children 12 years and over:
- 2 tablets (1 dose) every ½ hour to 1 hour or 4 tablets (2 doses) every hour as needed for diarrhea
- 2 tablets (1 dose) every ½ hour as needed for overindulgence (upset stomach, heartburn, indigestion, nausea)
- do not exceed 8 doses (16 tablets) in 24 hours
- use until diarrhea stops but not more than 2 days
- drink plenty of clear fluids to help prevent dehydration caused by diarrhea
- children under 12 years:ask a doctor

Other information

- each tablet contains: salicylate 102 mg
- Store at room temperature
- avoid excessive heat
- keep this carton for future reference on full labeling

Inactive ingredients

D&C Red No. 27, flavor, magnesium stearate, maltodextrin, microcrystalline cellulose, sorbitol, sucralose.

Questions or comments?

1-866-467-2748

Principal Display Panel

Compare to the active ingredient in Pepto-Bismol® Chewables*

Stomach Relief

Chewable Tablets

Upset Stomach Reliever/Antidiarrheal

Original flavor

5 Symptoms Digestive Relief:

- Heartburn
- Indigestion
- Nausea
- Upset Stomach
- Diarrhea

30 Chewable Tablets

TAMPER EVIDENT: DO NOT USE IF CARTON IS OPENED OR OF STRIP UNIT IS TORN, BROKEN OR SHOWS ANY SIGNS OF TAMPERING

*This product is not manufactured or distributed by Procter & Gamble Inc., the distributor of Pepto-Bismol® Chewables.

Distributed by: